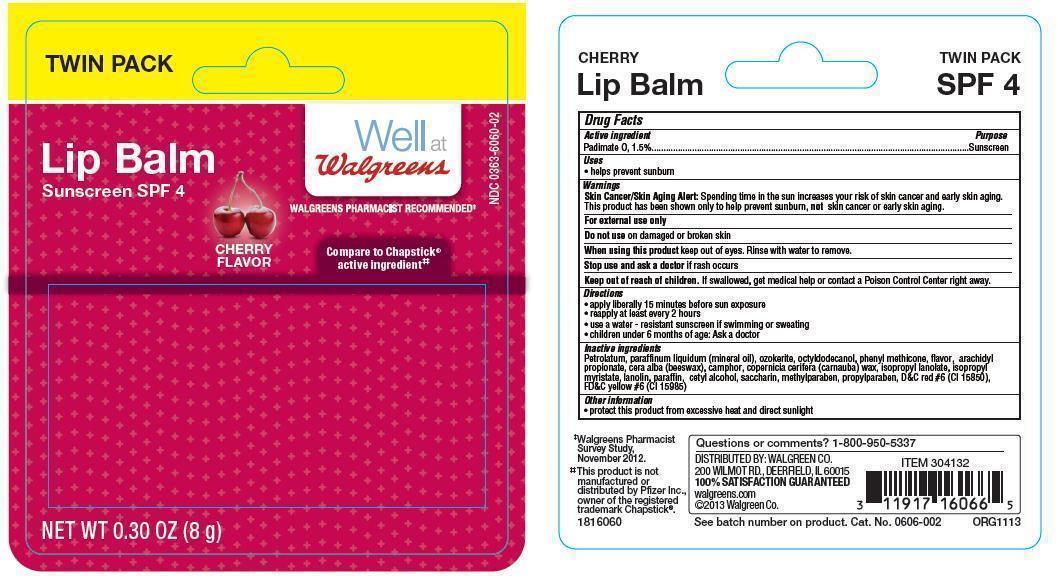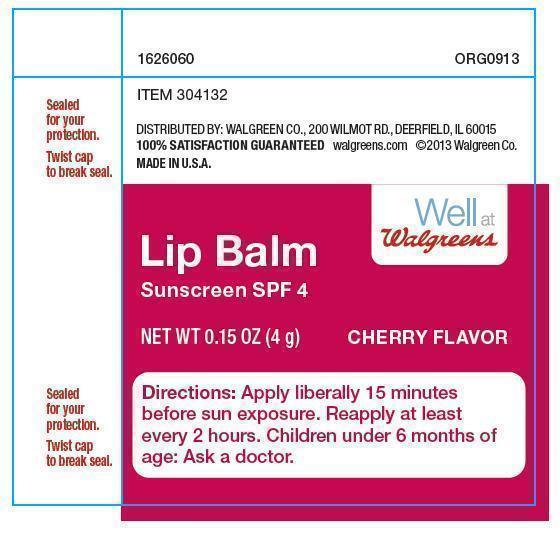 DRUG LABEL: Lip Balm Sunscreen SPF 4
NDC: 0363-6060 | Form: STICK
Manufacturer: Walgreen Co
Category: otc | Type: HUMAN OTC DRUG LABEL
Date: 20131115

ACTIVE INGREDIENTS: PADIMATE O 1.5 mg/1 g
INACTIVE INGREDIENTS: PETROLATUM; ARACHIDYL PROPIONATE; WHITE WAX; CAMPHOR (NATURAL); CARNAUBA WAX; CETYL ALCOHOL; D&C RED NO. 6; FD&C YELLOW NO. 6; ISOPROPYL MYRISTATE; LIGHT MINERAL OIL; METHYLPARABEN; OCTYLDODECANOL; PARAFFIN; PROPYLPARABEN; SACCHARIN; LANOLIN; PHENYL TRIMETHICONE

Drug Facts

Active ingredients

Padimate O, 1.5%

Purpose

Sunscreen

Uses

- Helps prevent sunburn

Warnings

Skin Cancer/Skin Aging Alert: Spending time in the sun increases your risk of skin cancer and early skin aging. This product has been shown only to help prevent sunburn, not skin cancer or early skin aging.

For external use only

Do not use on damaged or broken skin

When using this product, keep out of eyes. Rinse with water to remove.

Stop use and ask a doctor if rash occurs.

Keep out of reach of children. If swallowed, get medical help or contact a Poison Control Center right away.

Directions

- apply liberally 15 minutes before sun exposure
- reapply at least every 2 hours
- use a water-resistant sunscreen if swimming or sweating
- children under 6 months of age: Ask a doctor

Other information

- protect this product from excessive heat and direct sunlight

Inactive ingredients

Petrolatum, paraffinum liquidum (mineral oil), ozokerite, octyldodecanol, phenyl methicone, flavor, arachidyl propionate, cera alba (beeswax), camphor, copernicia cerifera (carnauba) wax, isopropyl lanolate, isopropyl myristate, lanolin, paraffin, cetyl alcohol, saccharin, methylparaben, propylparaben, D&C red #6 (CI 15850), FD&C yellow #6 (CI 15985)